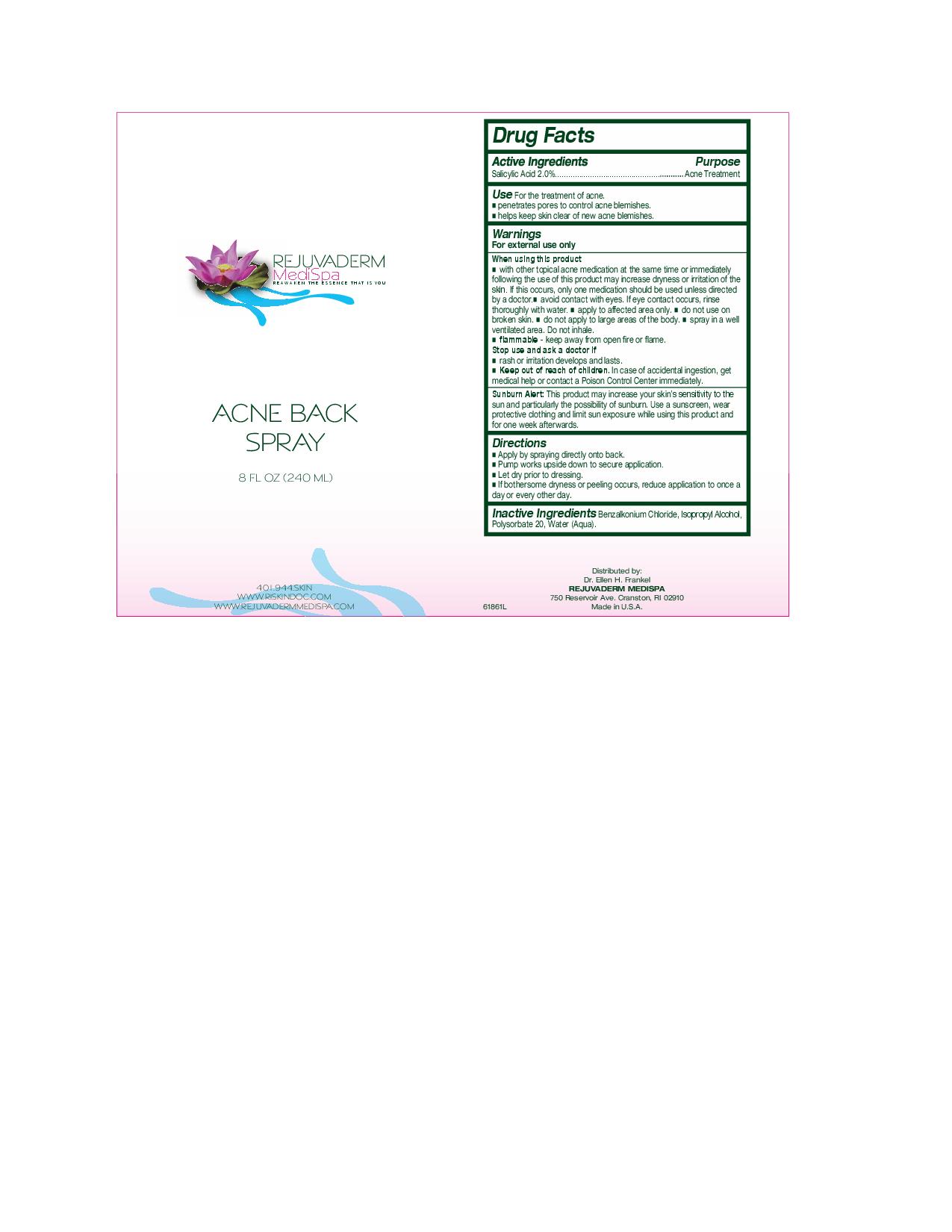 DRUG LABEL: Rejuvaderm MediSpa Acne Back 
NDC: 51325-400 | Form: SPRAY
Manufacturer: Ellen Frankle MD Inc.
Category: otc | Type: HUMAN OTC DRUG LABEL
Date: 20100720

ACTIVE INGREDIENTS: SALICYLIC ACID 4.8 mL/240 mL
INACTIVE INGREDIENTS: Benzalkonium chloride; Isopropyl alcohol; Polysorbate 20; Water

Rejuvaderm Medispa Acne back

Active Ingredients Purpose

Salicylic acid 2.0% Acne Treatment

INDICATIONS AND USAGE

Use For the treatment of acne.

- penetrates pores to control acne blemishes.
- helps keep skin clear of new acne blemishes.

Warnings

For external use only

When using this product

- with other topical acne medication at the same time or immediately following the use of this product may increase dryness or irritation of the skin. If this occurs, only one medication should be used unless directed by a doctor. avoid contact with eyes. If eye contact occurs, rinse thoroughly with water. apply to affected area only. do not use on broken skin. do not aply to large areas of the body. Spray in a well ventilated area. Do not inhale.
- flammable-keep away from open fire or flame.
  Stop use and ask a doctor if
- rash or irritation develops and lasts.

Sunburn Alert: this product may increase your skin's sensitivity to the sun and particularly the possibility of sunburn. Use a sunscreen, wear protective clothing and limit sun exposure while using this product and for one week afterwards.

Directions

- Apply byspraying directly onto back.
- Pump works upside down to secure application.
- Let dry prior to dressing.
- If bothersome dryness or peeling occurs, reduce application to once a day or every other day.

INACTIVE INGREDIENT

Inactive Ingredients Benzalkonium Chloride, Isopropyl Alcohol, Polysorbate 20, Water (Aqua).

PURPOSE

Acne treatment

Keep out of reach of children. In case of accidental ingestion, get medical help or contact a Poison Control Center immediately.

PACKAGE LABEL

Rejuvaderm Medispa

reawaken the essence that is you

acne back spray

8 fl oz. (240 ml)

401944skin

www.riskindoc.com

www.rejuvadermmedispa.com